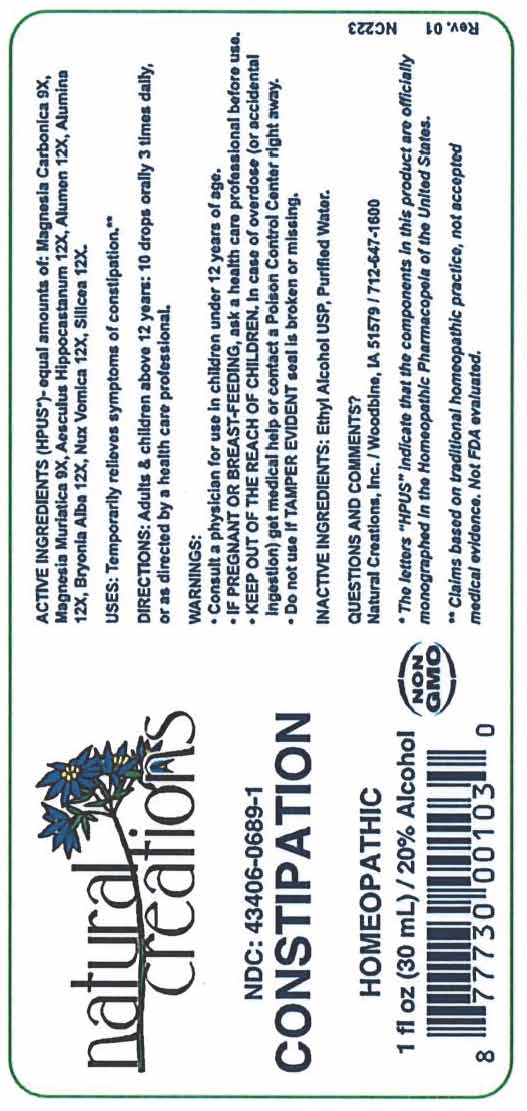 DRUG LABEL: CONSTIPATION
NDC: 43406-0689 | Form: LIQUID
Manufacturer: Natural Creations, Inc.
Category: homeopathic | Type: HUMAN OTC DRUG LABEL
Date: 20251121

ACTIVE INGREDIENTS: MAGNESIUM CARBONATE 9 [hp_X]/1 mL; MAGNESIUM CHLORIDE 9 [hp_X]/1 mL; HORSE CHESTNUT 12 [hp_X]/1 mL; POTASSIUM ALUM 12 [hp_X]/1 mL; ALUMINUM OXIDE 12 [hp_X]/1 mL; BRYONIA ALBA ROOT 12 [hp_X]/1 mL; STRYCHNOS NUX-VOMICA SEED 12 [hp_X]/1 mL; SILICON DIOXIDE 12 [hp_X]/1 mL
INACTIVE INGREDIENTS: WATER; ALCOHOL

CONSTIPATION

ACTIVE INGREDIENT

ACTIVE INGREDIENTS (HPUS*): Magnesia Carbonica 9X, Magnesia Muriatica 9X, Aesculus Hippocastanum 12X, Alumen 12X, Alumina 12X, Bryonia Alba 12X, Nux Vomica 12X, Silicea 12X

PURPOSE

USES: Temporarily relieves symptoms of constipation.**

KEEP OUT OF REACH OF CHILDREN

KEEP OUT OF THE REACH OF CHILDREN. In case of overdose (or accidental ingestion) get medical help or contact a Poison Control Center.

INDICATIONS AND USAGE

USES: Temporarily relieves symptoms of constipation.**

WARNING:

- Consult a physician for use in children under 12 years of age.
- IF PREGNANT OR BREAST-FEEDING, ask a health professional before use.
- KEEP OUT OF THE REACH OF CHILDREN. In case of overdose (or accidental ingestion) get medical help or contact a Poison Control Center right away.
- Do not use if TAMPER EVIDENT seal is broken or missing.

DOSAGE AND ADMINISTRATION

DIRECTIONS: Adults & children above 12 years: 10 drops orally 3 times daily, or as directed by a health care professional.

INACTIVE INGREDIENTS: Ethyl Alcohol USP, Purified Water.

Questions & Comments?

Natural Creations, Inc. / Woodbine, IA 51579 / 712-647-1600

REFERENCES

*The letters “HPUS” indicate the components in the product are officially monographed in the Homeopathic Pharmacopeia of the United States.

**Claims based on traditional homeopathic practice, not accepted medical evidence. Not FDA evaluated.

PACKAGE LABEL

NDC: 43406-0689-1

CONSTIPATION

HOMEOPATHIC

1 fl oz (30 mL) / 20% Alcohol

UPC: 877730001030